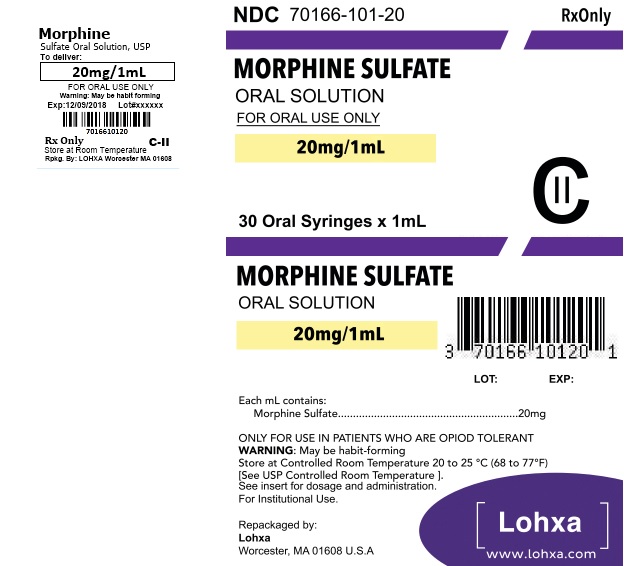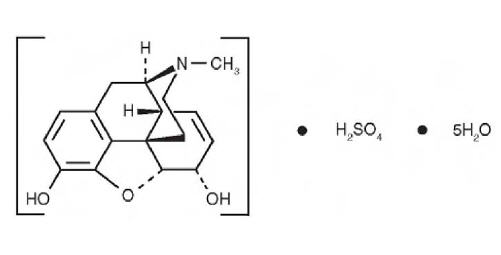 DRUG LABEL: Morphine Sulfate
NDC: 70166-101 | Form: SOLUTION, CONCENTRATE
Manufacturer: Lohxa
Category: prescription | Type: HUMAN PRESCRIPTION DRUG LABEL
Date: 20180612
DEA Schedule: CII

ACTIVE INGREDIENTS: MORPHINE SULFATE 100 mg/5 mL
INACTIVE INGREDIENTS: ANHYDROUS CITRIC ACID; EDETATE DISODIUM; GLYCERIN; METHYLPARABEN; PROPYLPARABEN; SODIUM BENZOATE; SORBITOL; FD&C GREEN NO. 3; WATER

HIGHLIGHTS OF PRESCRIBING INFORMATION

These highlights do not include all the information needed to use MORPHINE SULFATE ORAL SOLUTION safely and effectively. See full prescribing information for MORPHINE SULFATE ORAL SOLUTION.
MORPHINE SULFATE oral solution, CII
Initial U.S. Approval: 1941

WARNING: RISK OF MEDICATION ERRORS; ADDICTION, ABUSE, AND MISUSE; LIFE-THREATENING RESPIRATORY DEPRESSION; ACCIDENTAL INGESTION; NEONATAL OPIOID WITHDRAWAL SYNDROME; and RISKS FROM CONCOMITANT USE WITH BENZODIAZEPINES OR OTHER CNS DEPRESSANTS

WARNING: RISK OF MEDICATION ERRORS; ADDICTION, ABUSE, AND MISUSE; LIFE-THREATENING RESPIRATORY DEPRESSION; ACCIDENTAL INGESTION; NEONATAL OPIOID WITHDRAWAL SYNDROME; RISKS FROM CONCOMITANT USE WITH BENZODIAZEPINES OR OTHER CNS DEPRESSANTS

See full prescribing information for complete boxed warning.

- Ensure accuracy when prescribing, dispensing, and administering Morphine Sulfate Oral Solution. Dosing errors due to confusion between mg and mL, and other Morphine Sulfate Oral Solution of different concentrations can result in accidental overdose and death. (2.1, 5.1)
- Morphine Sulfate Oral Solution exposes users to risks of addiction, abuse, and misuse, which can lead to overdose and death. Assess patient’s risk before prescribing and monitor regularly for these behaviors and conditions. (5.2)
- Serious, life-threatening, or fatal respiratory depression may occur. Monitor closely, especially upon initiation or following a dose increase. (5.3)
- Accidental ingestion of Morphine Sulfate Oral Solution, especially by children, can result in a fatal overdose of morphine. (5.3)
- Prolonged use of Morphine Sulfate Oral Solution during pregnancy can result in neonatal opioid withdrawal syndrome, which may be life-threatening if not recognized and treated. If prolonged opioid use is required in a pregnant woman, advise the patient of the risk of neonatal opioid withdrawal syndrome and ensure that appropriate treatment will be available. (5.4)
- Concomitant use of opioids with benzodiazepines or other central nervous system (CNS) depressants, including alcohol, may result in profound sedation, respiratory depression, coma, and death. Reserve concomitant prescribing for use in patients for whom alternative treatment options are inadequate; limit dosages and durations to the minimum required; and follow patients for signs and symptoms of respiratory depression and sedation. (5.5, 7)

RECENT MAJOR CHANGES

Boxed Warning 12/2016

Indications and Usage (1) 12/2016

Dosage and Administration (2) 12/2016

Contraindications (4) 12/2016

Warnings and Precautions (5) 12/2016

1. INDICATIONS AND USAGE

Morphine Sulfate Oral Solution is an opioid agonist indicated for the management of acute and chronic pain in opiod-tolerant patients severe enough to require an opioid analgesic and for which alternative treatments are inadequate. (1)

Limitations of Use (1)

Because of the risks of addiction, abuse, and misuse with opioids, even at recommended doses, reserve Morphine Sulfate Oral Solution for use in patients for whom alternative treatment options [e.g., non-opioid analgesics or opioid combination products]:

- Have not been tolerated, or are not expected to be tolerated,
- Have not provided adequate analgesia, or are not expected to provide adequate analgesia

2. DOSAGE AND ADMINISTRATION

- Morphine Sulfate Oral Solution 100 mg per 5 mL (20 mg/mL) is for opioid-tolerant patients only. (2.1)
- Use the lowest effective dosage for the shortest duration consistent with individual patient treatment goals. (2.1)
- Individualize dosing based on the severity of pain, patient response, prior analgesic experience, and risk factors for addiction, abuse, and misuse. (2.1)
- Initiate treatment with 10 mg to 20 mg (0.5 mL to 1 mL) every 4 hours as needed. (2.2)
- Do not stop Morphine Sulfate Oral Solution abruptly in a physically dependent patient. (2.4)

3. DOSAGE FORMS AND STRENGTHS

Oral Solution: 100 mg/ 5 mL (20 mg/ mL) (3)

4. CONTRAINDICATIONS

- Significant respiratory depression. (4)
- Acute or severe bronchial asthma in an unmonitored setting or in absence of resuscitative equipment. (4) Concurrent use of monoamine oxidase inhibitors (MAOIs) or use of MAOIs within the last 14 days. (4)
- Known or suspected gastrointestinal obstruction, including paralytic ileus. (4)
- Hypersensitivity to morphine. (4)

5. WARNINGS AND PRECAUTIONS

- Life-Threatening Respiratory Depression in Patients with Chronic Pulmonary Disease or in Elderly, Cachectic, and Debilitated Patients: Monitor closely, particularly during initiation and titration. (5.3)
- Adrenal Insufficiency: If diagnosed, treat with physiologic replacement of corticosteroids, and wean patient off of the opioid. (5.7)
- Severe Hypotension: Monitor during dosage initiation and titration. Avoid use of Morphine Sulfate Oral Solution in patients with circulatory shock. (5.8)
- Risks of Use in Patients with Increased Intracranial Pressure, Brain Tumors, Head Injury, or Impaired Consciousness: Monitor for sedation and respiratory depression. Avoid use of Morphine Sulfate Oral Solution in patients with impaired consciousness or coma. (5.9)

6. ADVERSE REACTIONS

Most common adverse reactions are constipation, nausea, somnolence, lightheadedness, dizziness, sedation, vomiting, and sweating. (6)

To report SUSPECTED ADVERSE REACTIONS, contact Lannett Company, Inc. at 1-844-834-0530 or FDA at 1-800-FDA-1088 or www.fda.gov/medwatch

7. DRUG INTERACTIONS

- Serotonergic Drugs: Concomitant use may result in serotonin syndrome. Discontinue Morphine Sulfate Oral Solution if serotonin syndrome is suspected. (7)
- Mixed Agonist/Antagonist and Partial Agonist Opioid Analgesics: Avoid use with Morphine Sulfate Oral Solution because they may reduce analgesic effect of Morphine Sulfate Oral Solution or precipitate withdrawal symptoms. (7)

8. USE IN SPECIFIC POPULATIONS

- Pregnancy: May cause fetal harm. (8.1)

FULL PRESCRIBING INFORMATION

WARNING: RISK OF MEDICATION ERRORS; ADDICTION, ABUSE, AND MISUSE; LIFE-THREATENING RESPIRATORY DEPRESSION; ACCIDENTAL INGESTION; NEONATAL OPIOID WITHDRAWAL SYNDROME; and RISKS FROM CONCOMITANT USE WITH BENZODIAZEPINES OR OTHER CNS DEPRESSANTS

Risk of Medication Errors

Ensure accuracy when prescribing, dispensing, and administering Morphine Sulfate Oral Solution. Dosing errors due to confusion between mg and mL, and other Morphine Sulfate Oral Solutions of different concentrations can result in accidental overdose and death [see Dosage and Administration (2.1), Warnings and Precautions (5.1)] .

Addiction, Abuse, and Misuse

Morphine Sulfate Oral Solution exposes patients and other users to the risks of opioid addiction, abuse, and misuse, which can lead to overdose and death. Assess each patient’s risk prior to prescribing Morphine Sulfate Oral Solution, and monitor all patients regularly for the development of these behaviors and conditions [see Warnings and Precautions (5.2)] .

Life-Threatening Respiratory Depression

Serious, life-threatening, or fatal respiratory depression may occur with use of Morphine Sulfate Oral Solution. Monitor for respiratory depression, especially during initiation of Morphine Sulfate Oral Solution or following a dose increase [see Warnings and Precautions (5.3)].

Accidental Ingestion

Accidental ingestion of even one dose of Morphine Sulfate Oral Solution, especially by children, can result in a fatal overdose of morphine [see Warnings and Precautions (5.3)] .

Neonatal Opioid Withdrawal Syndrome

Prolonged use of Morphine Sulfate Oral Solution during pregnancy can result in neonatal opioid withdrawal syndrome, which may be life-threatening if not recognized and treated, and requires management according to protocols developed by neonatology experts. If opioid use is required for a prolonged period in a pregnant woman, advise the patient of the risk of neonatal opioid withdrawal syndrome and ensure that appropriate treatment will be available [see Warnings and Precautions (5.4)] .

Risks From Concomitant Use With Benzodiazepines Or Other CNS Depressants

Concomitant use of opioids with benzodiazepines or other central nervous system (CNS) depressants, including alcohol, may result in profound sedation, respiratory depression, coma, and death [see Warnings and Precautions (5.5), Drug Interactions (7)] .

- Reserve concomitant prescribing of Morphine Sulfate Oral Solution and benzodiazepines or other CNS depressants for use in patients for whom alternative treatment options are inadequate.
- Limit dosages and durations to the minimum required.
- Follow patients for signs and symptoms of respiratory depression and sedation.

RECENT MAJOR CHANGES

Boxed Warning 4/2016

Indications and Usage (1) 4/2016

Dosage and Administration (2) 4/2016

Contraindications (4) 4/2016

Warnings and Precautions (5) 4/2016

Adverse Reactions (6) 4/2016

Drug Interactions (7) 4/2016

Patient Counseling Information (17) 4/2016

1. INDICATIONS AND USAGE

Morphine Sulfate Oral Solution is indicated for the management of acute and chronic pain in opioid-tolerant patients severe enough to require an opioid analgesic and for which alternative treatments are inadequate.

Limitations of Use

Because of the risks of addiction, abuse, and misuse with opioids, even at recommended doses [see Warnings and Precautions (5.2)] , reserve Morphine Sulfate Oral Solution for use in patients for whom alternative treatment options [e.g., non-opioid analgesics or opioid combination products]:

- Have not been tolerated, or are not expected to be tolerated,
- Have not provided adequate analgesia, or are not expected to provide adequate analgesia

2. DOSAGE AND ADMINISTRATION

2.1 Important Dosage and Administration Instructions

Morphine Sulfate Oral Solution 100 mg per 5 mL (20 mg/mL) is for use in opioid-tolerant patients only who have already been receiving opioid therapy. Use this strength only for patients who have already been titrated to a stable analgesic regimen using lower strengths of morphine sulfate and who can benefit from use of a smaller volume of oral solution.

Patients considered to be opioid tolerant are those who are those receiving, for one week or longer, at least 60 mg oral morphine per day, 25 mcg transdermal fentanyl per hour, 30 mg oral oxycodone per day, 8 mg oral hydromorphone per day, 25 mg oral oxymorphone per day, 60 mg oral hydrocodone per day, or an equianalgesic dose of another opioid.

Ensure accuracy when prescribing, dispensing, and administering Morphine Sulfate Oral Solution to avoid dosing errors due to confusion between mg and mL, and with other morphine sulfate solutions of different concentrations, which could result in accidental overdose and death. Ensure the proper dose is communicated and dispensed. When writing prescriptions, include both the total dose in mg and the total dose in volume.

Always use the enclosed calibrated oral syringe when administering Morphine Sulfate Oral Solution 100 mg per 5 mL (20 mg/mL) to ensure the dose is measured and administered accurately.

Do not use household teaspoons or tablespoons to measure Morphine Sulfate Oral Solution, as using a tablespoon instead of a teaspoon could lead to overdosage.

- Use the lowest effective dosage for the shortest duration consistent with individual patient treatment goals [see Warnings and Precautions (5)] .
- Initiate the dosing regimen for each patient individually, taking into account the patient's severity of pain, patient response, prior analgesic treatment experience, and risk factors for addiction, abuse, and misuse [see Warnings and Precautions (5.2)] .
- Monitor patients closely for respiratory depression, especially within the first 24-72 hours of initiating therapy and following dosage increases with Morphine Sulfate Oral Solution and adjust the dosage accordingly [see Warnings and Precautions (5.3)] .

2.2 Initial Dosage

Initiating Treatment with Morphine Sulfate Oral Solution

Do not initiate treatment with Morphine Sulfate Oral Solution 100 mg per 5 mL (20 mg per mL) in patients who are opioid naïve. Select an alternate product with lower concentration. Initiate treatment with Morphine Sulfate Oral Solution in a dosing range of 10 to 20 mg every 4 hours as needed for pain.

Conversion from Parenteral Morphine to Morphine Sulfate Oral Solution

For conversion from parenteral to Morphine Sulfate Oral Solution, anywhere from 3 mg to 6 mg of oral morphine sulfate may be required to provide pain relief equivalent to 1 mg of parenteral morphine.

Conversion from Other Opioids to Morphine Sulfate Oral Solution

There is inter-patient variability in the potency of opioid drugs and opioid formulations. Therefore, a conservative approach is advised when determining the total daily dose of Morphine Sulfate Oral Solution. It is safer to underestimate a patient’s 24-hour Morphine Sulfate Oral Solution dosage than to overestimate the 24-hour Morphine Sulfate Oral Solution dosage and manage an adverse reaction due to overdose. Initiate treatment with Morphine Sulfate Oral Solution in a dosing range of 10 to 20 mg every 4 hours as needed for pain.

In converting patients from other opioids to morphine sulfate, close observation and adjustment of dosage based upon the patient’s response to morphine sulfate is imperative.

Conversion from Morphine Sulfate Oral Solution to Extended-Release Morphine

For a given dose, the same total amount of morphine sulfate is available from Morphine Sulfate Oral Solution and extended-release morphine formulations. The extended duration of release of morphine sulfate from extended-release formulations results in reduced maximum and increased minimum plasma morphine sulfate concentrations than with shorter acting morphine sulfate products. Conversion from Morphine Sulfate Oral Solution to the same total daily dose of extended-release formulation could lead to excessive sedation at peak serum levels. Therefore, conversion to extended-release morphine formulations must be accompanied by close observation for signs of excessive sedation and respiratory depression.

2.3 Titration and Maintenance of Therapy

Individually titrate Morphine Sulfate Oral Solution to a dose that provides adequate analgesia and minimizes adverse reactions. Continually reevaluate patients receiving Morphine Sulfate Oral Solution to assess the maintenance of pain control and the relative incidence of adverse reactions, as well as monitoring for the development of addiction, abuse, or misuse [see Warnings and Precautions (5.2)] . Frequent communication is important among the prescriber, other members of the healthcare team, the patient, and the caregiver/family during periods of changing analgesic requirements, including initial titration.

If the level of pain increases after dosage stabilization, attempt to identify the source of increased pain before increasing the Morphine Sulfate Oral Solution dosage. If unacceptable opioid-related adverse reactions are observed, consider reducing the dosage. Adjust the dosage to obtain an appropriate balance between management of pain and opioid-related adverse reactions.

2.4 Discontinuation of Morphine Sulfate Oral Solution

When a patient who has been taking Morphine Sulfate Oral Solution regularly and may be physically dependent no longer requires therapy with Morphine Sulfate Oral Solution, taper the dose gradually, by 25% to 50% every 2 to 4 days, while monitoring carefully for signs and symptoms of withdrawal. If the patient develops these signs or symptoms, raise the dose to the previous level and taper more slowly, either by increasing the interval between decreases, decreasing the amount of change in dose, or both. Do not abruptly discontinue Morphine Sulfate Oral Solution in a physically-dependent patient [see Warnings and Precautions (5.12), Drug Abuse and Dependence (9.3)].

3. DOSAGE FORMS AND STRENGTHS

Each mL of clear/colorless Morphine Sulfate Oral Solution contains 20 mg of morphine sulfate, USP. The concentration of this solution is 100 mg per 5 mL (20 mg per mL).

Each mL of clear/blue Morphine Sulfate Oral Solution contains 20 mg of morphine sulfate, USP. The concentration of this solution is 100 mg per 5 mL (20 mg per mL).

4. CONTRAINDICATIONS

Morphine Sulfate Oral Solution is contraindicated in patients with:

- Significant respiratory depression [see Warnings and Precautions (5.3)]
- Acute or severe bronchial asthma in an unmonitored setting or in the absence of resuscitative equipment [see Warnings and Precautions (5.6)]
- Concurrent use of monoamine oxidase inhibitors (MAOIs) or use of MAOIs within the last 14 days [see Warnings and Precautions (5.5), Drug Interactions (7))] .
- Known or suspected gastrointestinal obstruction, including paralytic ileus [see Warnings and Precautions (5.10)]
- Hypersensitivity to morphine (e.g., anaphylaxis) [see Adverse Reactions (6)]

5. WARNINGS AND PRECAUTIONS

5.1 Risk of Accidental Overdose and Death due to Medication Errors

Dosing errors can result in accidental overdose and death. Avoid dosing errors that may result from confusion between mg and mL and confusion with morphine sulfate solutions of different concentrations, when prescribing, dispensing, and administering Morphine Sulfate Oral Solution. Ensure that the dose is communicated clearly and dispensed accurately. Always use the enclosed calibrated oral syringe when administering Morphine Sulfate Oral Solution to ensure the dose is measured and administered accurately. A household teaspoon or tablespoon is not an adequate measuring device. Given the inexactitude of the household spoon measure and the possibility of using a tablespoon instead of a teaspoon, which could lead to overdosage, it is strongly recommended that caregivers obtain and use a calibrated measuring device. Health care providers should recommend a calibrated device that can measure and deliver the prescribed dose accurately, and instruct caregivers to use extreme caution in measuring the dosage.

5.2 Addiction, Abuse, and Misuse

Morphine Sulfate Oral Solution contains morphine, a Schedule II controlled substance. As an opioid, Morphine Sulfate Oral Solution exposes users to the risks of addiction, abuse, and misuse [see Drug Abuse and Dependence (9)].

Although the risk of addiction in any individual is unknown, it can occur in patients appropriately prescribed Morphine Sulfate Oral Solution. Addiction can occur at recommended dosages and if the drug is misused or abused.

Assess each patient’s risk for opioid addiction, abuse, or misuse prior to prescribing Morphine Sulfate Oral Solution, and monitor all patients receiving Morphine Sulfate Oral Solution for the development of these behaviors and conditions. Risks are increased in patients with a personal or family history of substance abuse (including drug or alcohol abuse or addiction) or mental illness (e.g., major depression). The potential for these risks should not, however, prevent the proper management of pain in any given patient. Patients at increased risk may be prescribed opioids such as Morphine Sulfate Oral Solution, but use in such patients necessitates intensive counseling about the risks and proper use of Morphine Sulfate Oral Solution along with intensive monitoring for signs of addiction, abuse, and misuse.

Opioids are sought by drug abusers and people with addiction disorders and are subject to criminal diversion. Consider these risks when prescribing or dispensing Morphine Sulfate Oral Solution. Strategies to reduce these risks include prescribing the drug in the smallest appropriate quantity and advising the patient on the proper disposal of unused drug [see Patient Counseling Information (17)] . Contact local state professional licensing board or state controlled substances authority for information on how to prevent and detect abuse or diversion of this product.

5.3 Life-Threatening Respiratory Depression

Serious, life-threatening, or fatal respiratory depression has been reported with the use of opioids, even when used as recommended. Respiratory depression, if not immediately recognized and treated, may lead to respiratory arrest and death. Management of respiratory depression may include close observation, supportive measures, and use of opioid antagonists, depending on the patient’s clinical status [see Overdosage (10)] . Carbon dioxide (CO2) retention from opioid-induced respiratory depression can exacerbate the sedating effects of opioids.

While serious, life-threatening, or fatal respiratory depression can occur at any time during the use of Morphine Sulfate Oral Solution, the risk is greatest during the initiation of therapy or following a dosage increase. Monitor patients closely for respiratory depression, especially within the first 24-72 hours of initiating therapy with and following dosage increases of Morphine Sulfate Oral Solution.

To reduce the risk of respiratory depression, proper dosing and titration of Morphine Sulfate Oral Solution are essential [see Dosage and Administration (2.3)] . Overestimating the Morphine Sulfate Oral Solution dosage when converting patients from another opioid product can result in a fatal overdose with the first dose.

Accidental ingestion of even one dose of Morphine Sulfate Oral Solution, especially by children, can result in respiratory depression and death due to an overdose of morphine.

Morphine Sulfate Oral Solution 100 mg per 5 mL (20 mg per mL) is for use in opioid-tolerant patients only. Administration of this formulation may cause fatal respiratory depression when administered to patients who are not tolerant to the respiratory depressant effects of opioids.

5.4 Neonatal Opioid Withdrawal Syndrome

Prolonged use of Morphine Sulfate Oral Solution during pregnancy can result in withdrawal in the neonate. Neonatal opioid withdrawal syndrome, unlike opioid withdrawal syndrome in adults, may be life-threatening if not recognized and treated, and requires management according to protocols developed by neonatology experts. Observe newborns for signs of neonatal opioid withdrawal syndrome and manage accordingly. Advise pregnant women using opioids for a prolonged period of the risk of neonatal opioid withdrawal syndrome and ensure that appropriate treatment will be available [see Use in Specific Populations (8.1), Patient Counseling Information (17)] .

5.5 Risks from Concomitant Use with Benzodiazepines or Other CNS Depressants

Profound sedation, respiratory depression, coma, and death may result from the concomitant use of Morphine Sulfate Oral Solution with benzodiazepines or other CNS depressants (e.g., non- benzodiazepine sedatives/hypnotics, anxiolytics, tranquilizers, muscle relaxants, general anesthetics, antipsychotics, other opioids, alcohol). Because of these risks, reserve concomitant prescribing of these drugs for use in patients for whom alternative treatment options are inadequate.

Observational studies have demonstrated that concomitant use of opioid analgesics and benzodiazepines increases the risk of drug-related mortality compared to use of opioid analgesics alone. Because of similar pharmacological properties, it is reasonable to expect similar risk with the concomitant use of other CNS depressant drugs with opioid analgesics [see Drug Interactions (7)] .

If the decision is made to prescribe a benzodiazepine or other CNS depressant concomitantly with an opioid analgesic, prescribe the lowest effective dosages and minimum durations of concomitant use. In patients already receiving an opioid analgesic, prescribe a lower initial dose of the benzodiazepine or other CNS depressant than indicated in the absence of an opioid, and titrate based on clinical response. If an opioid analgesic is initiated in a patient already taking a benzodiazepine or other CNS depressant, prescribe a lower initial dose of the opioid analgesic, and titrate based on clinical response. Follow patients closely for signs and symptoms of respiratory depression and sedation.

Advise both patients and caregivers about the risks of respiratory depression and sedation when Morphine Sulfate Oral Solution is used with benzodiazepines or other CNS depressants (including alcohol and illicit drugs). Advise patients not to drive or operate heavy machinery until the effects of concomitant use of the benzodiazepine or other CNS depressant have been determined. Screen patients for risk of substance use disorders, including opioid abuse and misuse, and warn them of the risk for overdose and death associated with the use of additional CNS depressants including alcohol and illicit drugs [see Drug Interactions (7) and Patient Counseling Information (17)] .

5.6 Life-Threatening Respiratory Depression in Patients with Chronic Pulmonary Disease or in Elderly, Cachectic, or Debilitated Patients

The use of Morphine Sulfate Oral Solution in patients with acute or severe bronchial asthma in an unmonitored setting or in the absence of resuscitative equipment is contraindicated.

Patients with Chronic Pulmonary Disease

Morphine Sulfate Oral Solution-treated patients with significant chronic obstructive pulmonary disease or cor pulmonale, and those with a substantially decreased respiratory reserve, hypoxia, hypercapnia, or pre-existing respiratory depression are at increased risk of decreased respiratory drive including apnea, even at recommended dosages of Morphine Sulfate Oral Solution [see Warnings and Precautions (5.3)].

Elderly, Cachectic, or Debilitated Patients

Life-threatening respiratory depression is more likely to occur in elderly, cachectic, or debilitated patients because they may have altered pharmacokinetics or altered clearance compared to younger, healthier patients [see Warnings and Precautions (5.3)] .

Monitor such patients closely, particularly when initiating and titrating Morphine Sulfate Oral Solution and when Morphine Sulfate Oral Solution is given concomitantly with other drugs that depress respiration [see Warnings and Precautions (5.3)] . Alternatively, consider the use of non-opioid analgesics in these patients.

5.7 Interaction with Monoamine Oxidase Inhibitors

Monoamine oxidase inhibitors (MAOIs) may potentiate the effects of morphine, including respiratory depression, coma, and confusion. Morphine Sulfate Oral Solution should not be used in patients taking MAOIs or within 14 days of stopping such treatment.

5.8 Adrenal Insufficiency

Cases of adrenal insufficiency have been reported with opioid use, more often following greater than one month of use. Presentation of adrenal insufficiency may include non-specific symptoms and signs including nausea, vomiting, anorexia, fatigue, weakness, dizziness, and low blood pressure. If adrenal insufficiency is suspected, confirm the diagnosis with diagnostic testing as soon as possible. If adrenal insufficiency is diagnosed, treat with physiologic replacement doses of corticosteroids. Wean the patient off of the opioid to allow adrenal function to recover and continue corticosteroid treatment until adrenal function recovers. Other opioids may be tried as some cases reported use of a different opioid without recurrence of adrenal insufficiency. The information available does not identify any particular opioids as being more likely to be associated with adrenal insufficiency.

5.9 Severe Hypotension

Morphine Sulfate Oral Solution may cause severe hypotension including orthostatic hypotension and syncope in ambulatory patients. There is increased risk in patients whose ability to maintain blood pressure has already been compromised by a reduced blood volume or concurrent administration of certain CNS depressant drugs (e.g., phenothiazines or general anesthetics) [see Drug Interactions (7)]. Monitor these patients forsigns of hypotension after initiating or titrating the dosage of Morphine Sulfate Oral Solution. In patients with circulatory shock, Morphine Sulfate Oral Solution may cause vasodilation that can further reduce cardiac output and blood pressure. Avoid the use of Morphine Sulfate Oral Solution in patients with circulatory shock.

5.10 Risks of Use in Patients with Increased Intracranial Pressure, Brain Tumors, Head Injury, or Impaired Consciousness

In patients who may be susceptible to the intracranial effects of CO2retention (e.g., those with evidence of increased intracranial pressure or brain tumors), Morphine Sulfate Oral Solution may reduce respiratory drive, and the resultant CO2 retention can further increase intracranial pressure. Monitor such patients for signs of sedation and respiratory depression, particularly when initiating therapy with Morphine Sulfate Oral Solution.

Opioids may also obscure the clinical course in a patient with a head injury. Avoid the use of Morphine Sulfate Oral Solution in patients with impaired consciousness or coma.

5.11 Risks of Use in Patients with Gastrointestinal Conditions

Morphine Sulfate Oral Solution is contraindicated in patients with known or suspected gastrointestinal obstruction, including paralytic ileus.

The morphine in Morphine Sulfate Oral Solution may cause spasm of the sphincter of Oddi. Opioids may cause increases in serum amylase. Monitor patients with biliary tract disease, including acute pancreatitis for worsening symptoms.

5.12 Increased Risk of Seizures in Patients with Convulsive or Seizure Disorders

The morphine in Morphine Sulfate Oral Solution may increase the frequency of seizures in patients with seizure disorders, and may increase the risk of seizures occuring in other clinical settings associated with seizures. Monitor patients with a history of seizure disorders for worsened seizure control during Morphine Sulfate Oral Solution therapy.

5.13 Withdrawal

Avoid the use of mixed agonist/antagonist (e.g, pentazocine, nalbuphine, and butorphanol) or partial agonist (e.g., buprenorphine) analgesics in patients who are receiving a full opioid agonist analgesic, including Morphine Sulfate Oral Solution. In these patients, mixed agonist/antagonist and partial agonist analgesics may reduce the analgesic effect and/or precipitate withdrawal symptoms.

When discontinuing Morphine Sulfate Oral Solution, gradually taper the dosage [see Dosage and Administration (2.4)] . Do not abruptly discontinue Morphine Sulfate Oral Solution [see Drug Abuse and Dependence (9.3)] .

5.14 Risks of Driving and Operating Machinery

Morphine Sulfate Oral Solution may impair the mental or physical abilities needed to perform potentially hazardous activities such as driving a car or operating machinery. Warn patients not to drive or operate dangerous machinery unless they are tolerant to the effects of Morphine Sulfate Oral Solution and know how they will react to the medication [see Patient Counseling Information (17)] .

6. ADVERSE REACTIONS

The following serious adverse reactions are described, or described in greater detail, in other sections:

- Addiction, Abuse, and Misuse [see Warnings and Precautions (5.2)]
- Life-Threatening Respiratory Depression [see Warnings and Precautions (5.3)]
- Neonatal Opioid Withdrawal Syndrome [see Warnings and Precautions (5.4)]
- Interactions with Benzodiazepine or Other CNS Depressants [see Warnings and Precautions (5.5)]
- Adrenal Insufficiency [see Warnings and Precautions (5.8)]
- Severe Hypotension [see Warnings and Precautions (5.9)]
- Gastrointestinal Adverse Reactions [see Warnings and Precautions (5.11)]
- Seizures [see Warnings and Precautions (5.12)]
- Withdrawal [see Warnings and Precautions (5.13)]

The following adverse reactions associated with the use of morphine were identified in clinical studies or postmarketing reports. Because some of these reactions were reported voluntarily from a population of uncertain size, it is not always possible to reliably estimate their frequency or establish a causal relationship to drug exposure.

Serious adverse reactions associated with morphine use included: respiratory depression, apnea, and to a lesser degree, circulatory depression, respiratory arrest, shock and cardiac arrest.

The common adverse reactions seen on initiation of therapy with morphine were dose-dependent and were typical opioid-related adverse reactions. The most frequent of these included constipation, nausea, and somnolence. Other commonly observed adverse reactions included: lightheadedness, dizziness, sedation, vomiting, and sweating. The frequency of these events depended upon several factors including clinical setting, the patient’s level of opioid tolerance, and host factors specific to the individual.

Other less frequently observed adverse reactions from opioid analgesics, including morphine sulfate included:

Body as a Whole: malaise, withdrawal syndrome

Cardiovascular System: bradycardia, hypertension, hypotension, palpitations, syncope, tachycardia

Digestive System: biliary pain, dyspepsia, dysphagia, gastroenteritis, abnormal liver function tests, rectal disorder, thirst

Endocrine: hypogonadism

Hemic and Lymphatic System: anemia, thrombocytopenia

Metabolic and Nutritional Disorders: edema, weight loss

Musculoskeletal: skeletal muscle rigidity

Nervous System: abnormal dreams, abnormal gait, agitation, amnesia, anxiety, ataxia, confusion, convulsions, coma, delirium, hallucinations, lethargy, nervousness, abnormal thinking, tremor, vasodilation, vertigo, headache

Respiratory System: hiccup, hypoventilation, voice alteration

Skin and Appendages: dry skin, urticaria, pruritus

Special Senses: amblyopia, eye pain, taste perversion

Urogenital System: abnormal ejaculation, dysuria, impotence, decreased libido, oliguria, urinary retention, anti-diuretic effect

Serotonin syndrome: Cases of serotonin syndrome, a potentially life-threatening condition, have been reported during concomitant use of opioids with serotonergic drugs.

Adrenal insufficiency: Cases of adrenal insufficiency have been reported with opioid use, more often following greater than one month of use.

Anaphylaxis: Anaphylaxis has been reported with ingredients contained in Morphine Sulfate Oral Solution.

Androgen deficiency: cases of androgen deficiency have occurred with chronic use of opioids [see Clinical Pharmacology (12.2)] .

7. DRUG INTERACTIONS

Table 1 includes clinically significant drug interactions with Morphine Sulfate Oral Solution.

Table 1: Clinically Significant Drug Interactions with Morphine Sulfate Oral Solution
Benzodiazepines and Other Central Nervous System (CNS) Depressants
Clinical Impact: | Due to additive pharmacologic effect, the concomitant use of benzodiazepines or other CNS depressants, including alcohol, increases the risk of respiratory depression, profound sedation, coma, and death.
Intervention: | Reserve concomitant prescribing of these drugs for use in patients for whom alternative treatment options are inadequate. Limit dosages and durations to the minimum required. Follow patients closely for signs of respiratory depression and sedation [see Warnings and Precautions (5.5)] .
Examples: | Benzodiazepines and other sedatives/hypnotics, anxiolytics, tranquilizers, muscle relaxants, general anesthetics, antipsychotics, other opioids, alcohol.
Serotonergic Drugs
Clinical Impact: | The concomitant use of opioids with other drugs that affect the serotonergic neurotransmitter system has resulted in serotonin syndrome .
Intervention: | If concomitant use is warranted, carefully observe the patient, particularly during treatment initiation and dose adjustment. Discontinue Morphine Sulfate Oral Solution if serotonin syndrome is suspected.
Examples: | Selective serotonin reuptake inhibitors (SSRIs), serotonin and norepinephrine reuptake inhibitors (SNRIs), tricyclic antidepressants (TCAs), triptans, 5-HT3 receptor antagonists, drugs that effect the serotonin neurotransmitter system (e.g., mirtazapine, trazodone, tramadol), monoamine oxidase (MAO) inhibitors (those intended to treat psychiatric disorders and also others, such as linezolid and intravenous methylene blue).
Monoamine Oxidase Inhibitors (MAOIs)
Clinical Impact: | MAOI interactions with opioids may manifest as serotonin syndrome or opioid toxicity (e.g., respiratory depression, coma) [see Warnings and Precautions (5.3, 5.7)] .
Intervention: | Do not use Morphine Sulfate Oral Solution in patients taking MAOIs or within 14 days of stopping such treatment.
Examples: | phenelzine, tranylcypromine, linezolid
Mixed Agonist/Antagonist and Partial Agonist Opioid Analgesics
Clinical Impact: | May reduce the analgesic effect of Morphine Sulfate Oral Solution and/or precipitate withdrawal symptoms.
Intervention: | Avoid concomitant use.
Examples: | butorphanol, nalbuphine, pentazocine, buprenorphine,
Muscle Relaxants
Clinical Impact: | Morphine may enhance the neuromuscular blocking action of skeletal muscle relaxants and produce an increased degree of respiratory depression.
Intervention: | Monitor patients for signs of respiratory depression that may be greater than otherwise expected and decrease the dosage of Morphine Sulfate Oral Solution and/or the muscle relaxant as necessary.
Cimetidine
Clinical Impact: | The concomitant use of morphine and cimetidine has been reported to precipitate apnea, confusion, and muscle twitching in an isolated report.
Intervention: | Monitor patients for increased respiratory and CNS depression when Morphine Sulfate Oral Solution is used concomitantly with cimetidine.
Diuretics
Clinical Impact: | Opioids can reduce the efficacy of diuretics by inducing the release of antidiuretic hormone.
Intervention: | Monitor patients for signs of diminished diuresis and/or effects on blood pressure and increase the dosage of the diuretic as needed.
Anticholinergic Drugs
Clinical Impact: | The concomitant use of anticholinergic drugs may increase risk of urinary retention and/or severe constipation, which may lead to paralytic ileus.
Intervention: | Monitor patients for signs of urinary retention or reduced gastric motility when Morphine Sulfate Oral Solution is used concomitantly with anticholinergic drugs.
P-Glycoprotein (P-gp) Inhibitors
Clinical Impact: | The concomitant use of P-gp inhibitors can increase the exposure to morphine by two-fold and can increase the risk of hypotension, respiratory depression, profound sedation, coma, and death.
Intervention: | Monitor patients for signs of respiratory depression that may be greater than otherwise expected and decrease the dosage of Morphine Sulfate Oral Solution and/or the P-gp inhibitor as necessary.
Examples: | quinidine, verapamil

8. USE IN SPECIFIC POPULATIONS

8.1 Pregnancy

Risk Summary

Prolonged use of opioid analgesics during pregnancy can cause neonatal opioid withdrawal syndrome [see Warnings and Precautions (5.3)] . There are no available data with Morphine Sulfate Oral Solution in pregnant women to inform a drug-associated risk for major birth defects and miscarriage. Published studies with morphine use during pregnancy have not reported a clear association with morphine and major birth defects [see Human Data]. In published animal reproduction studies, morphine administered subcutaneously during the early gestational period produced neural tube defects (i.e., exencephaly and cranioschisis) at 5 and 16 times the human daily dose of 60 mg based on body surface area (HDD) in hamsters and mice, respectively, lower fetal body weight and increased incidence of abortion at 0.4 times the HDD in the rabbit, growth retardation at 6 times the HDD in the rat, and axial skeletal fusion and cryptorchidism at 16 times the HDD in the mouse. Administration of morphine sulfate to pregnant rats during organogenesis and through lactation resulted in cyanosis, hypothermia, decreased brain weights, pup mortality, decreased pup body weights, and adverse effects on reproductive tissues at 3-4 times the HDD; and long-term neurochemical changes in the brain of offspring which correlate with altered behavioral responses that persist through adulthood at exposures comparable to and less than the HDD [see Animal Data]. Based on animal data, advise pregnant women of the potential risk to a fetus.

The estimated background risk of major birth defects and miscarriage for the indicated population is unknown. All pregnancies have a background risk of birth defect, loss, or other adverse outcomes. In the U.S. general population, the estimated background risk of major birth defects and miscarriage in clinically recognized pregnancies is 2-4% and 15-20%, respectively.

Clinical Considerations

Fetal/Neonatal Adverse Reactions

Prolonged use of opioid analgesics during pregnancy for medical or nonmedical purposes can result in physical dependence in the neonate and neonatal opioid withdrawal syndrome shortly after birth.

Neonatal opioid withdrawal syndrome presents as irritability, hyperactivity, and abnormal sleep pattern, high pitched cry, tremor, vomiting, diarrhea, and failure to gain weight. The onset, duration, and severity of the neonatal opioid withdrawal syndrome vary based on the specific opioid used, duration of use, timing and amount of last maternal use, and rate of elimination of the drug by the newborn. Observe newborns for symptoms of neonatal opioid withdrawal syndrome and manage accordingly [see Warnings and Precautions (5.4)] .

Labor or Delivery

Opioids cross the placenta and may produce respiratory depression and psycho-physiologic effects in neonates. An opioid antagonist, such as naloxone, must be available for reversal of opioid-induced respiratory depression in the neonate. Morphine Sulfate Oral Solution is not recommended for use in pregnant women during or immediately prior to labor, when other analgesic techniques are more appropriate. Opioid analgesics, including Morphine Sulfate Oral Solution, can prolong labor through actions which temporarily reduce the strength, duration, and frequency of uterine contractions. However, this effect is not consistent and may be offset by an increased rate of cervical dilation, which tends to shorten labor. Monitor neonates exposed to opioid analgesics during labor for signs of excess sedation and respiratory depression.

Data

Human Data

The results from a population-based prospective cohort, including 70 women exposed to morphine during the first trimester of pregnancy and 448 women exposed to morphine at any time during pregnancy, indicate no increased risk for congenital malformations. However, these studies cannot definitely establish the absence of any risk because of methodological limitations, including small sample size and non-randomized study design.

Animal Data

Formal reproductive and developmental toxicology studies for morphine have not been conducted. Exposure margins for the following published study reports are based on human daily dose of 60 mg morphine using a body surface area comparison (HDD).

Neural tube defects (exencephaly and cranioschisis) were noted following subcutaneous administration of morphine sulfate (35-322 mg/kg) on Gestation Day 8 to pregnant hamsters (4.7 to 43.5 times the HDD). A no adverse effect level was not defined in this study and the findings cannot be clearly attributed to maternal toxicity. Neural tube defects (exencephaly), axial skeletal fusions, and cryptorchidism were reported following a single subcutaneous (SC) injection of morphine sulfate to pregnant mice (100-500 mg/kg) on Gestation Day 8 or 9 at 200 mg/kg or greater (16 times the HDD) and fetal resorption at 400 mg/kg or higher (32 times the HDD). No adverse effects were noted following 100 mg/kg morphine in this model (8 times the HDD). In one study, following continuous subcutaneous infusion of doses greater than or equal to 2.72 mg/kg to mice (0.2 times the HDD), exencephaly, hydronephrosis, intestinal hemorrhage, split supraoccipital, malformed sternebrae, and malformed xiphoid were noted. The effects were reduced with increasing daily dose; possibly due to rapid induction of tolerance under these infusion conditions. The clinical significance of this report is not clear.

Decreased fetal weights were observed in pregnant rats treated with 20 mg/kg/day morphine sulfate (3.2 times the HDD) from Gestation Day 7 to 9. There was no evidence of malformations despite maternal toxicity (10% mortality). In a second rat study, decreased fetal weight and increased incidences of growth retardation were noted at 35 mg/kg/day (5.7 times the HDD) and there was a reduced number of fetuses at 70 mg/kg/day (11.4 times the HDD) when pregnant rats were treated with 10, 35, or 70 mg/kg/day morphine sulfate via continuous infusion from Gestation Day 5 to 20. There was no evidence of fetal malformations or maternal toxicity.

An increased incidence of abortion was noted in a study in which pregnant rabbits were treated with 2.5 (0.8 times the HDD) to 10 mg/kg morphine sulfate via subcutaneous injection from Gestation Day 6 to 10. In a second study, decreased fetal body weights were reported following treatment of pregnant rabbits with increasing doses of morphine (10-50 mg/kg/day) during the pre-mating period and 50 mg/kg/day (16 times the HDD) throughout the gestation period. No overt malformations were reported in either publication; although only limited endpoints were evaluated.

In published studies in rats, exposure to morphine during gestation and/or lactation periods is associated with: decreased pup viability at 12.5 mg/kg/day or greater (2 times the HDD); decreased pup body weights at 15 mg/kg/day or greater (2.4 times the HDD); decreased litter size, decreased absolute brain and cerebellar weights, cyanosis, and hypothermia at 20 mg/kg/day (3.2 times the HDD); alteration of behavioral responses (play, social-interaction) at 1 mg/kg/day or greater (0.2 times the HDD); alteration of maternal behaviors (e.g., decreased nursing and pup retrievals) in mice at 1 mg/kg or higher (0.08 times the HDD) and rats at 1.5 mg/kg/day or higher (0.2 times the HDD); and a host of behavioral abnormalities in the offspring of rats, including altered responsiveness to opioids at 4 mg/kg/day (0.7 times the HDD) or greater.

Fetal and/or postnatal exposure to morphine in mice and rats has been shown to result in morphological changes in fetal and neonatal brain and neuronal cell loss, alteration of a number of neurotransmitter and neuromodulator systems, including opioid and non-opioid systems, and impairment in various learning and memory tests that appear to persist into adulthood. These studies were conducted with morphine treatment usually in the range of 4 to 20 mg/kg/day (0.7 to 3.2 times the HDD).

Additionally, delayed sexual maturation and decreased sexual behaviors in female offspring at 20 mg/kg/day (3.2 times the HDD), and decreased plasma and testicular levels of luteinizing hormone and testosterone, decreased testes weights, seminiferous tubule shrinkage, germinal cell aplasia, and decreased spermatogenesis in male offspring were also observed at 20 mg/kg/day (3.2 times the HDD). Decreased litter size and viability were observed in the offspring of male rats that were intraperitoneally administered morphine sulfate for 1 day prior to mating at 25 mg/kg/day (4.1 times the HDD) and mated to untreated females. Decreased viability and body weight and/or movement deficits in both first and second generation offspring were reported when male mice were treated for 5 days with escalating doses of 120 to 240 mg/kg/day morphine sulfate (9.7 to 19.5 times the HDD) or when female mice treated with escalating doses of 60 to 240 mg/kg/day (4.9 to 19.5 times the HDD) followed by a 5-day treatment-free recovery period prior to mating. Similar multigenerational findings were also seen in female rats pre-gestationally treated with escalating doses of 10 to 22 mg/kg/day morphine (1.6 to 3.6 times the HDD).

8.2 Lactation

Risk Summary

Morphine is present in breast milk. Published lactation studies report variable concentrations of morphine in breast milk with administration of immediate-release morphine to nursing mothers in the early postpartum period with a milk-to-plasma morphine AUC ratio of 2.5:1 measured in one lactation study. However, there is insufficient information to determine the effects of morphine on the breastfed infant and the effects of morphine on milk production. Lactation studies have not been conducted with Morphine Sulfate Oral Solution, and no information is available on the effects of the drug on the breastfed infant or the effects of the drug on milk production.

The developmental and health benefits of breastfeeding should be considered along with the mother’s clinical need for Morphine Sulfate Oral Solution and any potential adverse effects on the breastfed infant from Morphine Sulfate Oral Solution or from the underlying maternal condition.

Clinical Considerations

Monitor infants exposed to Morphine Sulfate Oral Solution through breast milk for excess sedation and respiratory depression. Withdrawal symptoms can occur in breastfed infants when maternal administration of morphine is stopped, or when breastfeeding is stopped.

8.3 Females and Males of Reproductive Potential

Infertility

Chronic use of opioids may cause reduced fertility in females and males of reproductive potential. It is not known whether these effects on fertility are reversible [see Adverse Reactions (6), Clinical Pharmacology (12.2)].

In published animal studies, morphine administration adversely effected fertility and reproductive endpoints in male rats and prolonged estrus cycle in female rats [ See Nonclinical Toxicology (13) ].

8.4 Pediatric Use

The safety and effectiveness and the pharmacokinetics of Morphine Sulfate Oral Solution in pediatric patients below the age of 18 have not been established.

8.5 Geriatric Use

Elderly patients (aged 65 years or older) may have increased sensitivity to morphine. In general, use caution when selecting a dosage for an elderly patient, usually starting at the low end of the dosing range, reflecting the greater frequency of decreased hepatic, renal, or cardiac function and of concomitant disease or other drug therapy.

Respiratory depression is the chief risk for elderly patients treated with opioids, and has occurred after large initial doses were administered to patients who were not opioid-tolerant or when opioids were co-administered with other agents that depress respiration. Titrate the dosage of Morphine Sulfate Oral Solution slowly in geriatric patients and monitor closely for signs of central nervous system and respiratory depression [see Warnings and Precautions (5.6)] .

Morphine is known to be substantially excreted by the kidney, and the risk of adverse reactions to this drug may be greater in patients with impaired renal function. Because elderly patients are more likely to have decreased renal function, care should be taken in dose selection, and it may be useful to monitor renal function.

8.6 Hepatic Impairment

Morphine pharmacokinetics have been reported to be significantly altered in patients with cirrhosis. Start these patients with a lower than usual dosage of Morphine Sulfate Oral Solution and titrate slowly while monitoring for signs of respiratory depression, sedation, and hypotension [see Clinical Pharmacology (12.3)] .

8.7 Renal Impairment

Morphine pharmacokinetics are altered in patients with renal failure. Start these patients with a lower than usual dosage of Morphine Sulfate Oral Solution and titrate slowly while carefully monitoring for signs of respiratory depression, sedation, and hypotension [see Clinical Pharmacology (12.3)] .

9. DRUG ABUSE AND DEPENDENCE

9.1 Controlled Substance

Morphine Sulfate Oral Solution contains morphine, a Schedule II controlled substance.

9.2 Abuse

Morphine Sulfate Oral Solution contains morphine, a substance with a high potential for abuse similar to other opioids including codeine, fentanyl, hydrocodone, hydromorphone, methadone, oxycodone, oxymorphone, and tapentadol. Morphine Sulfate Oral Solution can be abused and is subject to misuse, addiction, and criminal diversion [see Warnings and Precautions (5.2)].

All patients treated with opioids require careful monitoring for signs of abuse and addiction, because use of opioid analgesic products carries the risk of addiction even under appropriate medical use.

Prescription drug abuse is the intentional non-therapeutic use of a prescription drug, even once, for its rewarding psychological or physiological effects.

Drug addiction is cluster of behavioral, cognitive, and physiological phenomena that develop after repeated substance use and includes: a strong desire to take the drug, difficulties in controlling its use, persisting in its use despite harmful consequences, a higher priority given to drug use than to other activities and obligations, increased tolerance, and sometimes a physical withdrawal.

“Drug-seeking” behavior is very common in persons with substance use disorders. Drug-seeking tactics include emergency calls or visits near the end of office hours, refusal to undergo appropriate examination, testing or referral, repeated “loss” of prescriptions, tampering with prescriptions, and reluctance to provide prior medical records or contact information for other treating physician(s). “Doctor shopping” (visiting multiple prescribers to obtain additional prescriptions) is common among drug abusers and people suffering from untreated addiction. Preoccupation with achieving adequate pain relief can be appropriate behavior in a patient with poor pain control.

Abuse and addiction are separate and distinct from physical dependence and tolerance. Health care providers should be aware that addiction may not be accompanied by concurrent tolerance and symptoms of physical dependence in all addicts. In addition, abuse of opioids can occur in the absence of true addiction.

Morphine Sulfate Oral Solution, like other opioids, can be diverted for non-medical use into illicit channels of distribution. Careful record-keeping of prescribing information, including quantity, frequency, and renewal requests, as required by state and federal law, is strongly advised.

Proper assessment of the patient, proper prescribing practices, periodic re-evaluation of therapy, and proper dispensing and storage are appropriate measures that help to limit abuse of opioid drugs.

Risks Specific to Abuse of Morphine Sulfate Oral Solution

Morphine Sulfate Oral Solution is for oral use only. Abuse of Morphine Sulfate Oral Solution poses a risk of overdose and death. The risk is increased with concurrent use of Morphine Sulfate Oral Solution with alcohol and other central nervous system depressants. Parenteral drug abuse is commonly associated with transmission of infectious diseases such as hepatitis and HIV.

9.3 Dependence

Both tolerance and physical dependence can develop during chronic opioid therapy. Tolerance is the need for increasing doses of opioids to maintain a defined effect such as analgesia (in the absence of disease progression or other external factors). Tolerance may occur to both the desired and undesired effects of drugs, and may develop at different rates for different effects.

Physical dependence results in withdrawal symptoms after abrupt discontinuation or a significant dosage reduction of a drug. Withdrawal also may be precipitated through the administration of drugs with opioid antagonist activity (e.g., naloxone, nalmefene), mixed agonist/antagonist analgesics (e.g., pentazocine, butorphanol, nalbuphine), or partial agonists (e.g., buprenorphine). Physical dependence may not occur to a clinically significant degree until after several days to weeks of continued opioid usage.

Morphine Sulfate Oral Solution should not be abruptly discontinued in a physically-dependent patient [see Dosage and Administration (2.4)]. If Morphine Sulfate Oral Solution is abruptly discontinued in a physically-dependent patient, a withdrawal syndrome may occur. Some or all of the following can characterize this syndrome: restlessness, lacrimation, rhinorrhea, yawning, perspiration, chills, myalgia, and mydriasis. Other signs and symptoms also may develop, including: irritability, anxiety, backache, joint pain, weakness, abdominal cramps, insomnia, nausea, anorexia, vomiting, diarrhea, or increased blood pressure, respiratory rate, or heart rate.

Infants born to mothers physically dependent on opioids will also be physically dependent and may exhibit respiratory difficulties and withdrawal signs [see Use in Specific Populations (8.1)] .

10. OVERDOSAGE

Clinical Presentation

Acute overdosage with Morphine Sulfate Oral Solution can be manifested by respiratory depression, somnolence progressing to stupor or coma, skeletal muscle flaccidity, cold and clammy skin, constricted pupils, and, in some cases, pulmonary edema, bradycardia, hypotension, partial or complete airway obstruction, atypical snoring, and death. Marked mydriasis rather than miosis may be seen with hypoxia in overdose situations [see Clinical Pharmacology (12.2)] .

Treatment of Overdose

In case of overdose, priorities are the reestablishment of a patent and protected airway and institution of assisted or controlled ventilation, if needed. Employ other supportive measures (including oxygen and vasopressors) in the management of circulatory shock and pulmonary edema as indicated. Cardiac arrest or arrhythmias will require advanced life-support techniques.

The opioid antagonists, naloxone or nalmefene, are specific antidotes to respiratory depression resulting from opioid overdose. For clinically significant respiratory or circulatory depression secondary to morphine overdose, administer an opioid antagonist. Opioid antagonists should not be administered in the absence of clinically significant respiratory or circulatory depression secondary to morphine overdose.

Because the duration of opioid reversal is expected to be less than the duration of action of morphine in Morphine Sulfate Oral Solution, carefully monitor the patient until spontaneous respiration is reliably reestablished. If the response to an opioid antagonist is suboptimal or only brief in nature, administer additional antagonist as directed by the product’s prescribing information.

In an individual physically dependent on opioids, administration of the recommended usual dosage of the antagonist will precipitate an acute withdrawal syndrome. The severity of the withdrawal symptoms experienced will depend on the degree of physical dependence and the dose of the antagonist administered. If a decision is made to treat serious respiratory depression in the physically dependent patient, administration of the antagonist should be initiated with care and by titration with smaller than usual doses of the antagonist.

11. DESCRIPTION

Morphine Sulfate Oral Solution is an opioid agonist, available as an oral solution 100 mg per 5 mL (20 mg/mL) for oral administration. The chemical name is 7,8-didehydro-4,5 α-epoxy-17 methylmorphinan-3,6 α-diol sulfate (2:1) (salt) pentahydrate. The molecular weight is 758. Its molecular formula is (C17H19NO3)2•H2SO4•5H2O, and it has the following chemical structure.

Morphine sulfate USP is an odorless, white crystalline powder with a bitter taste. It has a solubility of 1 in 21 parts of water and 1 in 1000 parts of alcohol, but is practically insoluble in chloroform or ether. The octanol:water partition coefficient of morphine is 1.42 at physiologic pH and the pKa is 7.9 for the tertiary nitrogen (the majority is ionized at pH 7.4).

The inactive ingredients in Morphine Sulfate Oral Solution (clear/colorless) include: anhydrous citric acid, edetate disodium dihydrate, glycerin, methylparaben, propylparaben, sodium benzoate, sorbitol, and purified water.

The inactive ingredients in Morphine Sulfate Oral Solution (clear/blue) include: anhydrous citric acid, edetate disodium dihydrate, glycerin, methylparaben, propylparaben, sodium benzoate, sorbitol, FD&C green no. 3, artificial raspberry flavor, artificial cream flavor, and purified water.

12. CLINICAL PHARMACOLOGY

12.1 Mechanism of Action

Morphine is a full opioid agonist and is relatively selective for the mu-opioid receptor, although it can bind to other opioid receptors at higher doses. The principal therapeutic action of morphine is analgesia. Like all full opioid agonists, there is no ceiling effect for analgesia with morphine. Clinically, dosage is titrated to provide adequate analgesia and may be limited by adverse reactions, including respiratory and CNS depression.

The precise mechanism of the analgesic action is unknown. However, specific CNS opioid receptors for endogenous compounds with opioid-like activity have been identified throughout the brain and spinal cord and are thought to play a role in the analgesic effects of this drug.

12.2 Pharmacodynamics

Effects on the Central Nervous System

Morphine produces respiratory depression by direct action on brain stem respiratory centers. The respiratory depression involves a reduction in the responsiveness of the brain stem respiratory centers to both increases in carbon dioxide tension and electrical stimulation.

Morphine causes miosis, even in total darkness. Pinpoint pupils are a sign of opioid overdose but are not pathognomonic (e.g., pontine lesions of hemorrhagic or ischemic origins may produce similar findings). Marked mydriasis rather than miosis may be seen due to hypoxia in overdose situations.

Effects on the Gastrointestinal Tract and Other Smooth Muscle

Morphine causes a reduction inmotility associated with an increase in smooth muscle tone in the antrum of the stomach and duodenum. Digestionof food in the small intestine is delayed and propulsive contractions are decreased. Propulsive peristalticwaves in the colon are decreased, while tone is increased to the point of spasm, resulting in constipation. Other opioid-induced effects may include a reduction in biliary and pancreatic secretions, spasm of thesphincter of Oddi, and transient elevations in serum amylase.

Effects on the Cardiovascular System

Morphine produces peripheral vasodilation which may result in orthostatic hypotensionor syncope. Manifestations of histamine release and/or peripheral vasodilation may include pruritus, flushing, red eyes and sweating and/or orthostatic hypotension.

Effects on the Endocrine System

Opioids inhibit the secretion of adrenocorticotropic hormone (ACTH), cortisol, and luteinizing hormone (LH) in humans [see Adverse Reactions (6)] . They also stimulate prolactin, growth hormone (GH) secretion, and pancreatic secretion of insulin and glucagon.

Chronic use of opioids may influence the hypothalamic-pituitary-gonadal axis, leading to androgen deficiency that may manifest as low libido, impotence, erectile dysfunction, amenorrhea, or infertility. The causal role of opioids in the clinical syndrome of hypogonadism is unknown because the various medical, physical, lifestyle, and psychological stressors that may influence gonadal hormone levels have not been adequately controlled for in studies conducted to date [see Adverse Reactions (6)] .

Effects on the Immune System

Opioids have been shown to have a variety of effects on components of the immune system in in vitro and animal models. The clinical significance of these findings is unknown. Overall, the effects of opioids appear to be modestly immunosuppressive.

Concentration–Efficacy Relationships

The minimum effective analgesic concentration will vary widely among patients, especially among patients who have been previously treated with potent agonist opioids. The minimum effective analgesic concentration of morphine for any individual patient may increase over time due to an increase in pain, the development of a new pain syndrome and/or the development of analgesic tolerance [see Dosage and Administration (2)] .

Concentration–Adverse Reaction Relationships

There is a relationship between increasing morphine plasma concentration and increasing frequency of dose-related opioid adverse reactions such as nausea, vomiting, CNS effects, and respiratory depression. In opioid-tolerant patients, the situation may be altered by the development of tolerance to opioid-related adverse reactions [see Dosage and Administration (2.1, 2.2, 2.4)] .

12.3 Pharmacokinetics

Absorption

Morphine, when administered as morphine sulfate, is about two-thirds absorbed from the gastrointestinal tract with the maximum analgesic effect occurring 60 minutes post-administration. The oral bioavailability of morphine, when administered as morphine sulfate, is less than 40% and shows large inter-individual variability due to extensive pre-systemic metabolism.

Food Effects

Presence of food is not expected to significantly impact absorption of morphine from Morphine Sulfate Oral Solution 100 mg per 5 mL (20 mg per mL). The concurrent intake of a high-fat, high-calorie meal enhanced the extent of absorption (about 16% increase in AUC), reduced the rate of absorption (about 25% decrease in Cmax), and delayed the Tmax (from 0.58 to 0.75 h) of morphine from the Morphine Sulfate Oral Solution 100 mg per 5 mL (20 mg per mL).

Distribution

Once absorbed, morphine is distributed to skeletal muscle, kidneys, liver, intestinal tract, lungs, spleen and brain. Although the primary site of action is the CNS, only small quantities cross the blood-brain barrier. Morphine also crosses the placental membranes and has been found in breast milk. The volume of distribution of morphine is approximately 1 to 6 L/kg, and morphine is 20 to 35% reversibly bound to plasma proteins.

Elimination

Metabolism

The major pathway of morphine detoxification is conjugation, either with D-glucuronic acid to produce glucuronides or with sulfuric acid to produce morphine-3-etheral sulfate. While a small fraction (less than 5%) of morphine is demethylated, virtually all morphine is converted by hepatic metabolism to the morphine-3-glucuronide (M3G) and morphine-6-glucuronide (M6G) metabolites (about 50% and 15%, respectively). M6G has been shown to have analgesic activity but crosses the blood-brain barrier poorly, while M3G has no significant analgesic activity.

Excretion

Most of a dose of morphine sulfate is excreted in urine as M3G and M6G, with elimination of morphine occurring primarily as renal excretion of M3G. Approximately 10% of the dose is excreted unchanged in urine. A small amount of glucuronide conjugates are excreted in bile, with minor enterohepatic recycling. Seven to 10% of administered morphine sulfate is excreted in the feces.The mean adult plasma clearance is approximately 20 to 30 mL/min/kg. The effective terminal half-life of morphine sulfate after IV administration is reported to be approximately 2 hours. In some studies involving longer periods of plasma sampling, a longer terminal half-life of morphine sulfate of about 15 hours was reported.

Specific Populations

Race/Ethnicity

There may be some pharmacokinetic differences associated with race. In one published study, Chinese subjects given intravenous morphine sulfate had a higher clearance when compared to Caucasian subjects (1852 +/- 116 mL/min compared to 1495 +/- 80 mL/min).

Sex

While evidence of greater post-operative morphine sulfate consumption in men compared to women is present in the literature, clinically significant differences in analgesic outcomes and pharmacokinetic parameters have not been consistently demonstrated. Some studies have shown an increased sensitivity to the adverse effects of morphine, including respiratory depression, in women compared to men.

Hepatic Impairment

Morphine pharmacokinetics are altered in patients with cirrhosis. Clearance was found to decrease with a corresponding increase in half-life. The M3G and M6G to morphine AUC ratios also decreased in these subjects, indicating diminished metabolic activity. Adequate studies of the pharmacokinetics of morphine in patients with severe hepatic impairment have not been conducted.

Renal Impairment

Morphine pharmacokinetics are altered in patients with renal failure. The AUC is increased and clearance is decreased and the metabolites, M3G and M6G, may accumulate to much higher plasma levels in patients with renal failure as compared to patients with normal renal function. Adequate studies of the pharmacokinetics of morphine in patients with severe renal impairment have not been conducted.

13. NONCLINICAL TOXICOLOGY

13.1 Carcinogenesis, Mutagenesis, Impairment of Fertility

Carcinogenesis

Long-term studies in animals to evaluate the carcinogenic potential of morphine have not been conducted.

Mutagenesis

No formal studies to assess the mutagenic potential of morphine have been conducted. In the published literature, morphine was found to be mutagenic in vitro increasing DNA fragmentation in human T-cells. Morphine was reported to be mutagenic in the in vivo mouse micronucleus assay and positive for the induction of chromosomal aberrations in mouse spermatids and murine lymphocytes. Mechanistic studies suggest that the in vivo clastogenic effects reported with morphine in mice may be related to increases in glucocorticoid levels produced by morphine in this species. In contrast to the above positive findings, in vitro studies in the literature have also shown that morphine did not induce chromosomal aberrations in human leukocytes or translocations or lethal mutations in Drosophila.

Impairment of Fertility

No formal nonclinical studies to assess the potential of morphine to impair fertility have been conducted.

Several nonclinical studies from the literature have demonstrated adverse effects on male fertility in the rat from exposure to morphine. One study in which male rats were administered morphine sulfate subcutaneously prior to mating (up to 30 mg/kg twice daily) and during mating (20 mg/kg twice daily) with untreated females, a number of adverse reproductive effects including reduction in total pregnancies and higher incidence of pseudopregnancies at 20 mg/kg/day (3.2 times the HDD) were reported.

Studies from the literature have also reported changes in hormonal levels in male rats (i.e. testosterone, luteinizing hormone) following treatment with morphine at 10 mg/kg/day or greater (1.6 times the HDD).

Female rats that were administered morphine sulfate intraperitoneally prior to mating exhibited prolonged estrous cycles at 10 mg/kg/day (1.6 times the HDD).

Exposure of adolescent male rats to morphine has been associated with delayed sexual maturation and following mating to untreated females, smaller litters, increased pup mortality, and/or changes in reproductive endocrine status in adult male offspring have been reported (estimated 5 times the plasma levels at the HDD).

16. HOW SUPPLIED/STORAGE AND HANDLING

Morphine Sulfate Oral Solution 100 mg per 5 mL (20 mg per mL) is a clear/blue solution, supplied as:

NDC 70166-101-02: 30, Overwrapped, 0.125mL prefilled unit dose oral syringe

NDC 70166-101-05: 30, Overwrapped, 0.25mL prefilled unit dose oral syringe

NDC 70166-101-10: 30, Overwrapped, 0.5mL prefilled unit dose oral syringe

NDC 70166-101-20: 30, Overwrapped, 1mL prefilled unit dose oral syringe

Store at Controlled Room Temperature, 15° to 30°C (59° to 86°F) [See USP Controlled Room Temperature.].

Protect from moisture.

17. PATIENT COUNSELING INFORMATION

Advise the patient to read the FDA-approved patient labeling (Medication Guide and Instructions for Use).

Medication Errors

Advise patients that Morphine Sulfate Oral Solution is available in 100 mg per 5 mL (20 mg/mL) concentration. Inform patients about which concentration they have been prescribed and provide detailed instruction on how to measure and take the correct dose of Morphine Sulfate Oral Solution, and to always use the enclosed measuring device when administering Morphine Sulfate Oral Solution to ensure that the dose is measured and administered accurately [see Warnings and Precautions (5.1)] .

If the prescribed concentration is changed, instruct patients on how to correctly measure the new dose to avoid errors which could result in accidental overdose and death.

Addiction, Abuse, and Misuse

Inform patients that the use of Morphine Sulfate Oral Solution, even when taken as recommended, can result in addiction, abuse, and misuse, which can lead to overdose and death [see Warnings and Precautions (5.2)]. Instruct patients not to share Morphine Sulfate Oral Solution with others and to take steps to protect Morphine Sulfate Oral Solution from theft or misuse.

Life-Threatening Respiratory Depression

Inform patients of the risk of life-threatening respiratory depression, including information that the risk is greatest when starting Morphine Sulfate Oral Solution or when the dosage is increased, and that it can occur even at recommended dosages [see Warnings and Precautions (5.3)] . Advise patients how to recognize respiratory depression and to seek medical attention if breathing difficulties develop.

Accidental Ingestion

Inform patients that accidental ingestion, especially by children, may result in respiratory depression or death [see Warnings and Precautions (5.3)] . Instruct patients to take steps to store Morphine Sulfate Oral Solution securely and to dispose of unused Morphine Sulfate Oral Solution by flushing down the toilet.

Interactions with Benzodiazepines and Other CNS Depressants

Inform patients and caregivers that potentially fatal additive effects may occur if Morphine Sulfate Oral Solution is used with benzodiazepines or other CNS depressants, including alcohol, and not to use these concomitantly unless supervised by a healthcare provider [see Warnings and Precautions (5.5), Drug Interactions (7)].

Serotonin Syndrome

Inform patients that opioids could cause a rare but potentially life-threatening condition resulting from concomitant administration of serotonergic drugs. Warn patients of the symptoms of serotonin syndrome and to seek medical attention right away if symptoms develop. Instruct patients to inform their physicians if they are taking, or plan to take serotonergic medications [see Drug Interactions (7)] .

MAOI Interaction

Inform patients not to take Morphine Sulfate Oral Solution while using any drugs that inhibit monoamine oxidase. Patients should not start MAOIs while taking Morphine Sulfate Oral Solution [see Warnings and Precatuions (5.7), Drug Interacrtions (7)] .

Adrenal Insufficiency

Inform patients that opioids could cause adrenal insufficiency, a potentially life-threatening condition. Adrenal insufficiency may present with non-specific symptoms and signs such as nausea, vomiting, anorexia, fatigue, weakness, dizziness, and low blood pressure. Advise patients to seek medical attention if they experience a constellation of these symptoms [see Warnings and Precautions (5.8)] .

Important Administration Instructions

Instruct patients how to properly take Morphine Sulfate Oral Solution.

- Advise patients to always use the enclosed calibrated oral syringe when administering Morphine Sulfate Oral Solution 100 mg per 5 mL (20 mg per mL) to ensure the dose is measured and administered accurately [see Dosage and Administration (2.1), Warnings and Precautions (5.1)].

- Advise patients never to use household teaspoons or tablespoons to measure Morphine Sulfate Oral Solution.
- Inform patients that the 100 mg per 5 mL (20 mg/mL) formulation is only for patients who are already receiving opioid-therapy and have demonstrated opioid-tolerance. Use of this formulation may cause fatal respiratory depression when administered to patients who have not had previous exposure to opioids [see Indications and Usage (1), Dosage and Administration (2.2)].
- Advise patients not to adjust the dose of Morphine Sulfate Oral Solution without consulting with a physician or other healthcare professional.

- If patients have been receiving treatment with Morphine Sulfate Oral Solution for more than a few weeks and cessation of therapy is indicated, counsel them on the importance of safely tapering the dose as abrupt discontinuation of the medication could precipitate withdrawal symptoms. Provide a dose schedule to accomplish a gradual discontinuation of the medication [ see Dosage and Administration (2.4) ].

Hypotension

Inform patients that Morphine Sulfate Oral Solution may cause orthostatic hypotension and syncope. Instruct patients how to recognize symptoms of low blood pressure and how to reduce the risk of serious consequences should hypotension occur (e.g., sit or lie down, carefully rise from a sitting or lying position) [see Warnings and Precautions (5.9)] .

Anaphylaxis

Inform patients that anaphylaxis have been reported with ingredients contained in Morphine Sulfate Oral Solution. Advise patients how to recognize such a reaction and when to seek medical attention [see Contraindications (4), Adverse Reactions (6)].

Pregnancy

Neonatal Opioid Withdrawal Syndrome

Inform female patients of reproductive potential that prolonged use of Morphine Sulfate Oral Solution during pregnancy can result in neonatal opioid withdrawal syndrome, which may be life-threatening if not recognized and treated [see Warnings and Precautions (5.4), Use in Specific Populations (8.1)].

Embryo-Fetal Toxicity

Inform female patients of reproductive potential that Morphine Sulfate Oral Solution can (or may) cause fetal harm and to inform their healthcare provider of a known or suspected pregnancy [see Use in Specific Populations (8.1)].

Lactation

Advise nursing mothers to monitor infants for increased sleepiness (more than usual), breathing difficulties, or limpness. Instruct nursing mothers to seek immediate medical care if they notice these signs [see Use in Specific Populations (8.2)] .

Infertility

Inform patients that chronic use of opioids may cause reduced fertility. It is not known whether these effects on fertility are reversible [see Use in Specific Populations (8.3)] .

Driving or Operating Heavy Machinery

Inform patients that Morphine Sulfate Oral Solution may impair the ability to perform potentially hazardous activities such as driving a car or operating heavy machinery. Advise patients not to perform such tasks until they know how they will react to the medication [see Warnings and Precautions (5.14)] .

Constipation

Advise patients of the potential for severe constipation, including management instructions and when to seek medical attention [see Adverse Reactions (6)] .

Disposal of Unused Morphine Sulfate Oral Solution

Advise patients to destroy the unused oral solution by flushing down the toilet.

Distributed by:
Lannett Company, Inc.
Philadelphia, PA 19154

Made in the USA

Revised 12/2016

11-138

MEDICATION GUIDE

Morphine (mȯr-ˌfēn) Sulfate Oral Solution (CII)

Morphine Sulfate Oral Solution is:

- A strong prescription pain medicine that contains an opioid (narcotic) that is used to manage short term (acute) and long term (chronic) pain.
- Severe enough to require an opioid pain medicine, in people who are already regularly using opioid pain medicine, when other pain treatments such as non-opioid pain medicines do not treat your pain well enough, or you cannot tolerate them.
- An opioid pain medicine that can put you at risk for overdose and death. Even if you take your dose correctly as prescribed you are at risk for opioid addiction, abuse, and misuse that can lead to death.

Important information about Morphine Sulfate Oral Solution:

- Get emergency help right away if you take too much Morphine Sulfate Oral Solution (overdose). When you first start taking Morphine Sulfate Oral Solution, when your dose is changed, or if you take too much (overdose), serious or life-threatening breathing problems that can lead to death may occur.
- Taking Morphine Sulfate Oral Solution with other opioid medicines, benzodiazepines, alcohol, or other central nervous system depressants (including street drugs) can cause severe drowsiness, decreased awareness, breathing problems, coma, and death.
- Never give anyone else your Morphine Sulfate Oral Solution. They could die from taking it. Store Morphine Sulfate Oral Solution away from children and in a safe place to prevent stealing or abuse. Selling or giving away Morphine Sulfate Oral Solution is against the law.

Do not take Morphine Sulfate Oral Solution if you have:

- severe asthma, trouble breathing, or other lung problems.
- a bowel blockage or have narrowing of the stomach or intestines.
- are allergic to morphine, morphine salts or any of the ingredients in Morphine Sulfate Oral Solution.

Before taking Morphine Sulfate Oral Solution, tell your healthcare provider if you have a history of:

- head injury, seizures
- problems urinating
- liver, kidney, thyroid problems
- pancreas or gallbladder problems
- abuse of street or prescription drugs, alcohol addiction, or mental health problems.

Tell your healthcare provider if you are:

- pregnant or planning to become pregnant. Prolonged use of Morphine Sulfate Oral Solution during pregnancy can cause withdrawal symptoms in your newborn baby that could be life-threatening if not recognized and treated.
- breastfeeding. Morphine Sulfate Oral Solution passes into breast milk and may harm your baby.
- taking prescription or over-the-counter medicines, vitamins, or herbal supplements. Taking Morphine Sulfate Oral Solution with certain other medicines can cause serious side effects that could lead to death.

When taking Morphine Sulfate Oral Solution:

- Do not change your dose. Take Morphine Sulfate Oral Solution exactly as prescribed by your healthcare provider. Use the lowest dose possible for the shortest time needed.
- See the detailed Instructions for Use for information about how to take Morphine Sulfate Oral Solution.
- Always use the enclosed calibrated oral syringe that comes with Morphine Sulfate Oral Solution to correctly measure your dose. Never use a household teaspoon or tablespoon to measure Morphine Sulfate Oral Solution.
- Take your prescribed dose every 4 hours as needed. Do not take more than your prescribed dose. If you miss a dose, take your next dose at your usual time.
- Call your healthcare provider if the dose you are taking does not control your pain.
- If you have been taking Morphine Sulfate Oral Solution regularly, do not stop taking Morphine Sulfate Oral Solution without talking to your healthcare provider.
- After you stop taking Morphine Sulfate Oral Solution, flush the unused oral solution down the toilet.

While taking Morphine Sulfate Oral Solution DO NOT:

- Drive or operate heavy machinery, until you know how Morphine Sulfate Oral Solution affects you. Morphine Sulfate Oral Solution can make you sleepy, dizzy, or lightheaded.
- Drink alcohol or use prescription or over-the-counter medicines that contain alcohol. Using products containing alcohol during treatment with Morphine Sulfate Oral Solution may cause you to overdose and die.

The possible side effects of Morphine Sulfate Oral Solution:

- constipation, nausea, sleepiness, vomiting, tiredness, headache, dizziness, abdominal pain. Call your healthcare provider if you have any of these symptoms and they are severe.

Get emergency medical help if you have:

- trouble breathing, shortness of breath, fast heartbeat, chest pain, swelling of your face, tongue, or throat, extreme drowsiness, light-headedness when changing positions, feeling faint, agitation, high body temperature, trouble walking, stiff muscles, or mental changes such as confusion.

These are not all the possible side effects of Morphine Sulfate Oral Solution. Call your doctor for medical advice about side effects. You may report side effects to FDA at 1-800-FDA-1088. For more information go to dailymed.nlm.nih.gov

Distributed by: Lannett Company, Inc., Philadelphia, PA 19154

www.lannett.com or call1-844-834-0530

This Medication Guide has been approved by the U.S. Food and Drug Administration.

Issued: 12/2016

11-139

Patient Instructions for Use

Morphine Sulfate (mȯr-ˌfēn) (CII)

Oral Solution 100 mg per 5 mL (20 mg per mL)

Oral Syringe

Important information about measuring Morphine Sulfate Oral Solution:

- Always use the oral syringe provided with your Morphine Sulfate Oral Solution to make sure you measure the right amount.
- Measure the dose of medicine from the widest part of the plunger.

PRINCIPAL DISPLAY PANEL — 1mL Pre-Filled Syringe

NDC 70166-101-20

MORPHINE SULFATE CII
ORAL SOLUTION

100 mg per 5 mL (20 mg/mL)

ONLY FOR USE IN PATIENTS
WHO ARE OPIOID TOLERANT

Rx Only